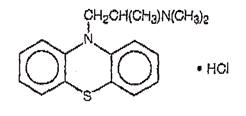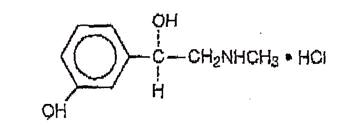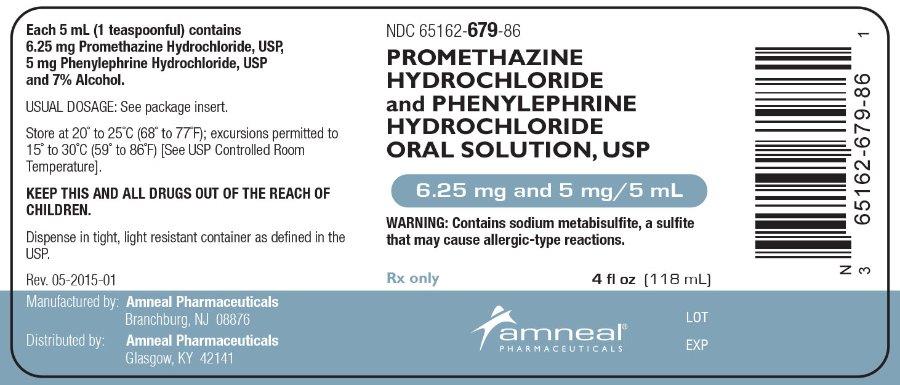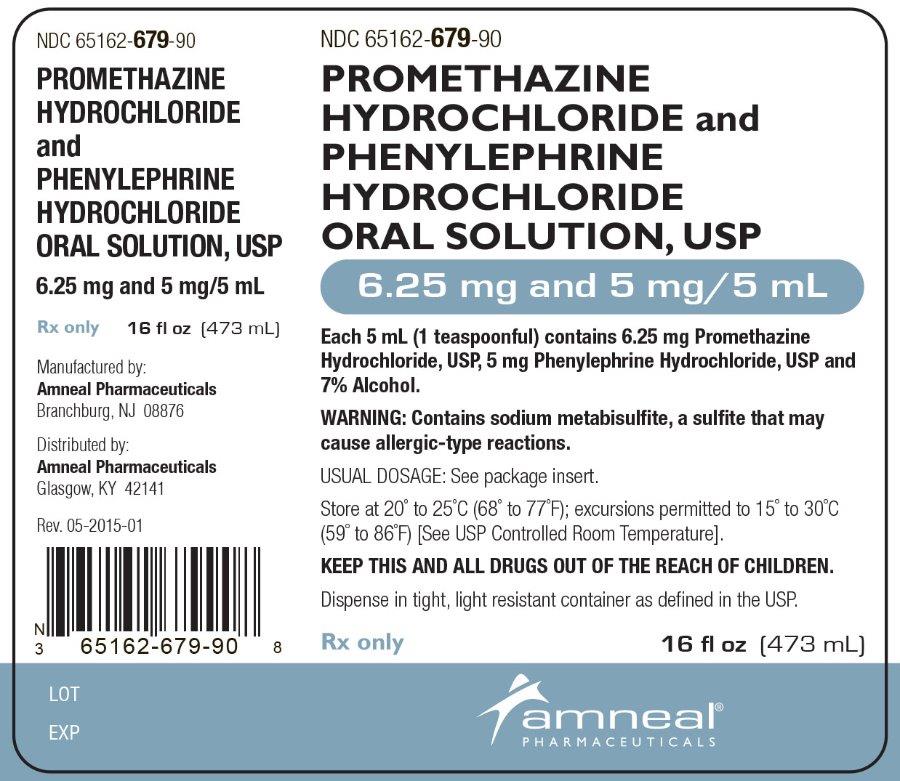 DRUG LABEL: Promethazine Hydrochloride and Phenylephrine Hydrochloride
NDC: 65162-679 | Form: SOLUTION
Manufacturer: Amneal Pharmaceuticals LLC
Category: prescription | Type: HUMAN PRESCRIPTION DRUG LABEL
Date: 20241030

ACTIVE INGREDIENTS: PROMETHAZINE HYDROCHLORIDE 6.25 mg/5 mL; PHENYLEPHRINE HYDROCHLORIDE 5 mg/5 mL
INACTIVE INGREDIENTS: ALCOHOL; ASCORBIC ACID; CITRIC ACID MONOHYDRATE; EDETATE DISODIUM; GLYCERIN; METHYLPARABEN; WATER; SACCHARIN SODIUM; SODIUM BENZOATE; SODIUM CITRATE; SODIUM METABISULFITE; SUCROSE

PROMETHAZINE HYDROCHLORIDE AND PHENYLEPHRINE HYDROCHLORIDE ORAL SOLUTION, USP
6.25 mg and 5 mg/5 mL
Rx Only

DESCRIPTION

Each 5 mL (one teaspoonful), for oral administration contains: Promethazine hydrochloride, USP 6.25 mg; phenylephrine hydrochloride, USP 5 mg. Alcohol 7%.

Inactive Ingredients: alcohol, ascorbic acid, caramel color, citric acid, edetate disodium, glycerin, methylparaben, natural & artificial citrus flavor, purified water, saccharin sodium, sodium benzoate, sodium citrate, sodium metabisulfite and sucrose.

Promethazine hydrochloride, USP, a phenothiazine derivative, is chemically designated as (±)-10-[2-(Dimethylamino)propyl] phenothiazine monohydrochloride.

Promethazine hydrochloride, USP occurs as a white to faint yellow, practically odorless, crystalline powder which slowly oxidizes and turns blue on prolonged exposure to air. It is soluble in water and freely soluble in alcohol. It has a molecular weight of 320.88, a molecular formula of C17H20N2S•HCl and the following structural formula:

Phenylephrine hydrochloride, USP is a sympathomimetic amine salt which is chemically designated as (-)-m-Hydroxy-α-[(methylamino)methyl]benzyl alcohol hydrochloride. It occurs as white or nearly white crystals, having a bitter taste. It is freely soluble in water and alcohol. Phenylephrine hydrochloride, USP is subject to oxidation and must be protected from light and air. It has a molecular weight of 203.67, a molecular formula of C9H13NO2•HCl, and the following structural formula:

CLINICAL PHARMACOLOGY

Promethazine:

Promethazine is a phenothiazine derivative which differs structurally from the antipsychotic phenothiazines by the presence of a branched side chain and no ring substitution. It is thought that this configuration is responsible for its relative lack (1/10 that of chlorpromazine) of dopamine antagonist properties.

Promethazine is an H1 receptor blocking agent. In addition to its antihistaminic action, it provides clinically useful sedative and antiemetic effects.

Promethazine is well absorbed from the gastrointestinal tract. Clinical effects are apparent within 20 minutes after oral administration and generally last four to six hours, although they may persist as long as 12 hours. Promethazine is metabolized by the liver to a variety of compounds; the sulfoxides of promethazine and N-demethylpromethazine are the predominant metabolites appearing in the urine.

Phenylephrine:

Phenylephrine is a potent postsynaptic α-receptor agonist with little effect on β-receptors of the heart. Phenylephrine has no effect on β-adrenergic receptors of the bronchi or peripheral blood vessels. A direct action at receptors accounts for the greater part of its effects, only a small part being due to its ability to release norepinephrine.

Therapeutic doses of phenylephrine mainly cause vasoconstriction. Phenylephrine increases resistance and, to a lesser extent, decreases capacitance of blood vessels. Total peripheral resistance is increased, resulting in increased systolic and diastolic blood pressure. Pulmonary arterial pressure is usually increased, and renal blood flow is usually decreased. Local vasoconstriction and hemostasis occur following topical application or infiltration of phenylephrine into tissues. The main effect of phenylephrine on the heart is bradycardia; it produces a positive inotropic effect on the myocardium in doses greater than those usually used therapeutically. Rarely, the drug may increase the irritability of the heart, causing arrhythmias. Cardiac output is decreased slightly. Phenylephrine increases the work of the heart by increasing peripheral arterial resistance.

Phenylephrine has a mild central stimulant effect.

Following oral administration or topical application of phenylephrine to the mucosa, constriction of blood vessels in the nasal mucosa relieves nasal congestion associated with allergy or head colds. Following oral administration, nasal decongestion may occur within 15 or 20 minutes and may persist for up to 4 hours.

Phenylephrine is irregularly absorbed from and readily metabolized in the gastrointestinal tract. Phenylephrine is metabolized in the liver and intestine by monoamine oxidase. The metabolites and their route and rate of excretion have not been identified. The pharmacologic action of phenylephrine is terminated at least partially by uptake of the drug into tissues.

INDICATIONS AND USAGE

Promethazine hydrochloride and phenylephrine hydrochloride oral solution, USP is indicated for the temporary relief of upper respiratory symptoms, including nasal congestion, associated with allergy or the common cold.

CONTRAINDICATIONS

Promethazine is contraindicated in comatose states, and in individuals known to be hypersensitive or to have had an idiosyncratic reaction to promethazine or to other phenothiazines.

Antihistamines are contraindicated for use in the treatment of lower respiratory tract symptoms, including asthma.

Phenylephrine is contraindicated in patients with hypertension or with peripheral vascular insufficiency (ischemia may result with risk of gangrene or thrombosis of compromised vascular beds). Phenylephrine should not be used in patients known to be hypersensitive to the drug or in those receiving a monoamine oxidase inhibitor (MAOI).

WARNINGS

Promethazine hydrochloride should not be used in pediatric patients less than 2 years of Age because of the potential for fatal respiratory depression.

Postmarketing cases of respiratory depression, including fatalities, have been reported with use of promethazine hydrochloride in pediatric patients less than 2 years of age. A wide range of weight-based doses of promethazine hydrochloride have results in respiratory depression in these patients.

Caution should be exercised when administering promethazine hydrochloride to pediatric patients 2 years of age and older. It is recommended that the lowest effective dose of promethazine hydrochloride be used in pediatric patients 2 years of age and older and concomitant administration of other drugs with respiratory depressant effects be avoided.

Sulfite Sensitivity:

Promethazine Hydrochloride and Phenylephrine Hydrochloride Oral Solution contains sodium metabisulfite, a sulfite that may cause allergic-type reactions including anaphylactic symptoms and life-threatening or less severe asthmatic episodes in certain susceptible people. The overall prevalence of sulfite sensitivity in the general population is unknown and probably low. Sulfite sensitivity is seen more frequently in asthmatic than in nonasthmatic people.

Promethazine:

CNS Depression- Promethazine may impair the mental and/or physical abilities required for the performance of potentially hazardous tasks, such as driving a vehicle or operating machinery. The impairment may be amplified by concomitant use of other central nervous-system depressants such as alcohol, sedatives/hypnotics (including barbiturates), narcotics, narcotic analgesics, general anesthetics, tricyclic antidepressants, and tranquilizers; therefore such agents should either be eliminated or given in reduced dosage in the presence of promethazine HCl (see PRECAUTIONS-Information for Patients and Drug Interactions).

Respiratory Depression -

Promethazine may lead to potentially fatal respiratory depression.

Use of Promethazine in patients with compromised respiratory function (e.g., COPD, sleep apnea) should be avoided.

Lower Seizure Threshold - Promethazine may lower seizure threshold. It should be used with caution in persons with seizure disorders or in persons who are using concomitant medications, such as narcotics or local anesthetics, which may also affect seizure threshold.

Bone-Marrow Depression - Promethazine should be used with caution in patients with bone-marrow depression. Leukopenia and agranulocytosis have been reported, usually when promethazine HCl has been used in association with other known marrow-toxic agents.

Neuroleptic Malignant Syndrome -

A potentially fatal symptom complex sometimes referred to as Neuroleptic Malignant Syndrome (NMS) has been reported in association with promethazine HCl alone or in combination with antipsychotic drugs. Clinical manifestations of NMS are hyperpyrexia, muscle rigidity, altered mental status and evidence of autonomic instability (irregular pulse or blood pressure, tachycardia, diaphoresis and cardiac dysrhythmias).

The diagnostic evaluation of patients with this syndrome is complicated. In arriving at a diagnosis, it is important to identify cases where the clinical presentation includes both serious medical illness (e.g. pneumonia, systemic infection, etc.) and untreated or inadequately treated extrapyramidal signs and symptoms (EPS). Other important considerations in the differential diagnosis include central anticholinergic toxicity, heat stroke, drug fever and primary central nervous system (CNS) pathology.

The management of NMS should include 1) immediate discontinuation of promethazine HCl, antipsychotic drugs, if any, and other drugs not essential to concurrent therapy, 2) intensive symptomatic treatment and medical monitoring, and 3) treatment of any concomitant serious medical problems for which specific treatments are available. There is no general agreement about specific pharmacological treatment regimens for uncomplicated NMS.

Since recurrences of NMS have been reported with phenothiazines, the reintroduction of promethazine HCl should be carefully considered.

Use in Pediatric Patients

Promethazine products are contraindicated for use in pediatric patients less than two years of age.

Caution should be exercised when administering promethazine products to pediatric patients 2 years of age and older because of the potential for fatal respiratory depression. Respiratory depression and apnea, sometime associated with death, are strongly associated with promethazine products and are not directly related to individualized weight-based dosing, which might otherwise permit safe administration. Concomitant administration of promethazine products with other respiratory depressants has an association with respiratory depression, and sometimes death, in pediatric patients.

Antiemetics are not recommended for treatment of uncomplicated vomiting in pediatric patients, and their use should be limited to prolonged vomiting of known etiology. The extrapyramidal symptoms which can occur secondary to promethazine hydrochloride administration may be confused with the CNS signs of undiagnosed primary disease, e.g., encephalopathy or Reye’s syndrome. The use of promethazine products should be avoided in pediatric patients whose signs and symptoms may suggest Reye’s syndrome or other hepatic diseases.

Excessively large dosages of antihistamines, including promethazine hydrochloride, in pediatric patients may cause sudden death (see OVERDOSAGE). Hallucinations and convulsions have occurred with therapeutic doses and overdoses of promethazine hydrochloride in pediatric patients. In pediatric patients who are acutely ill associated with dehydration there is an increased susceptibility to dystonias with the use of promethazine HCl.

Other Considerations

Administration of promethazine has been associated with reported cholestatic jaundice.

Phenylephrine:

Because phenylephrine is an adrenergic agent, it should be given with caution to patients with thyroid diseases, diabetes mellitus, and heart disease or those receiving tricyclic antidepressants.

Men with symptomatic, benign prostatic hypertrophy can experience urinary retention when given oral nasal decongestants.

Phenylephrine can cause a decrease in cardiac output, and extreme caution should be used when administering the drug parenterally or orally to patients with arteriosclerosis, to elderly individuals, and/or to patients with initially poor cerebral or coronary circulation.

Phenylephrine should be used with caution in patients taking diet preparations, such as amphetamines or phenylpropanolamine, because synergistic adrenergic effects could result in serious hypertensive response and possible stroke.

PRECAUTIONS

Animal reproduction studies have not been conducted with the drug combination - promethazine and phenylephrine. It is not known whether this drug combination can cause fetal harm when administered to a pregnant woman or can affect reproduction capacity. Promethazine and phenylephrine should be given to a pregnant woman only if clearly needed.

General:

Drugs having anticholinergic properties should be used with caution in patients with narrow-angle glaucoma, prostatic hypertrophy, stenosing peptic ulcer, pyloroduodenal obstruction, and bladder-neck obstruction.

Promethazine should be used cautiously in persons with cardiovascular disease or impairment of liver function.

Phenylephrine should be used with caution in patients with cardiovascular disease, particularly hypertension.

Information For Patients:

Patients should be advised to measure promethazine hydrochloride and phenylephrine hydrochloride oral solution with accurate measuring device. A household teaspoon is not an accurate measuring device and could lead to overdosage, especially when a half teaspoon is measured. A pharmacist can recommend an appropriate measuring device and can provide instructions for measuring the correct dose.

Promethazine and phenylephrine may cause marked drowsiness or may impair the mental and/or physical abilities required for the performance of potentially hazardous tasks, such as driving a vehicle or operating machinery. Ambulatory patients should be told to avoid engaging in such activities until it is known that they do not become drowsy or dizzy from promethazine and phenylephrine therapy. Children should be supervised to avoid potential harm in bike riding or in other hazardous activities.

The concomitant use of alcohol or other central nervous system depressants, including narcotic analgesics, sedatives, hypnotics, and tranquilizers, may have an additive effect and should be avoided or their dosage reduced.

Patients should be advised to report any involuntary muscle movements.

Avoid prolonged exposure to the sun.

Drug Interactions:

Promethazine

CNS Depressants - Promethazine may increase, prolong, or intensify the sedative action of other central-nervous system depressants, such as alcohol, sedatives/hypnotics (including barbiturates), narcotics, narcotic analgesics, general anesthetics, tricylic antidepressants, and tranquilizers; therefore, such agents should be avoided or administered in reduced dosage to patients receiving promethazine HCl. When given concomitantly with promethazine, the dose of barbiturates should be reduced by at least one-half, and the dose of narcotics should be reduced by one-quarter to one-half. Dosage must be individualized. Excessive amounts of promethazine HCl relative to a narcotic may lead to restlessness and motor hyperactivity in the patient with pain; these symptoms usually disappear with adequate control of the pain.

Epinephrine - Because of the potential for promethazine to reverse epinephrine's vasopressor effect, epinephrine should NOT be used to treat hypotension associated with promethazine overdose.

Anticholinergics - Concomitant use of other agents with anticholinergic properties should be undertaken with caution.

Monoamine oxidase inhibitors (MAOI) - Drug interactions, including an increased incidence of extrapyramidal effects, have been reported when some MAOI and phenothiazines are used concomitantly.

Phenylephrine

Drug

Phenylephrine with prior administration of monoamine oxidase inhibitors (MAOI).

Effect

Cardiac pressor response potentiated.

May cause acute hypertensive crisis.

Drug

Phenylephrine with tricyclic antidepressants.

Effect

Pressor response increased.

Drug

Phenylephrine with ergot alkaloids.

Effect

Excessive rise in blood pressure.

Drug

Phenylephrine with bronchodilator sympathomimetic agents and with epinephrine or other sympathomimetics.

Effect

Tachycardia or other arrhythmias may occur.

Drug

Phenylephrine with atropine sulfate

Effect

Reflex bradycardia blocked; pressor response enhanced.

Drug

Phenylephrine with prior administration of propranolol or other β -adrenergic blockers.

Effect

Cardiostimulating effects blocked.

Drug

Phenylephrine with prior administration of phentolamine or other α-adrenergic blockers.

Effect

Pressor response decreased.

Drug

Phenylephrine with diet preparations, such as amphetamines or phenylpropanolamine.

Effect

Synergistic adrenergic response.

Drug/Laboratory Test Interactions:

The following laboratory tests may be affected in patients who are receiving therapy with promethazine hydrochloride.

Pregnancy Tests:

Diagnostic pregnancy tests based on immunological reactions between HCG and anti-HCG may result in false-negative or false-positive interpretations.

Glucose Tolerance Test:

An increase in blood glucose has been reported in patients receiving promethazine.

Carcinogenesis, Mutagenesis, Impairment of Fertility:

Promethazine:

Long-term animal studies have not been performed to assess the carcinogenic potential of promethazine, nor are there other animal or human data concerning carcinogenicity, mutagenicity, or impairment of fertility with this drug.

Promethazine was nonmutagenic in the Salmonella test system of Ames.

Phenylephrine:

A study which followed the development of cancer in 143,574 patients over a four-year period indicated that in 11,981 patients who received phenylephrine (systemic or topical), there was no statistically significant association between the drug and cancer at any or all sites.

Long-term animal studies have not been performed to assess the carcinogenic potential of phenylephrine, nor are there other animal or human data concerning mutagenicity.

A study of the effects of adrenergic drugs on ovum transport in rabbits indicated that treatment with phenylephrine did not alter incidence of pregnancy; the number of implantations was significantly reduced when high doses of the drug were used.

Pregnancy:

Teratogenic Effects - Pregnancy category C

Promethazine:

Teratogenic effects have not been demonstrated in rat-feeding studies at doses of 6.25 and 12.5 mg/kg of promethazine HCl. These doses are from approximately 2.1 to 4.2 times the maximum recommended total daily dose of promethazine for a 50-kg subject, depending upon the indication for which the drug is prescribed. Daily doses of 25 mg/kg intraperitoneally have been found to produce fetal mortality in rats.

Specific studies to test the action of the drug on parturition, lactation, and development of the animal neonate were not done, but a general preliminary study in rats indicated no effect on these parameters. Although antihistamines have been found to produce fetal mortality in rodents, the pharmacological effects of histamine in the rodent do not parallel those in man. There are no adequate and well-controlled studies of promethazine in pregnant women.

Phenylephrine:

A study in rabbits indicated that continued moderate overexposure to phenylephrine (3 mg/day) during the second half of pregnancy (22nd day of gestation to delivery) may contribute to perinatal wastage, prematurity, premature labor, and possibly fetal anomalies; when phenylephrine (3 mg/day) was given to rabbits during the first half of pregnancy (3rd day after mating for seven days), a significant number gave birth to litters of low birth weight. Another study showed that phenylephrine was associated with anomalies of aortic arch and with ventricular septal defect in the chick embryo.

Promethazine and phenylephrine should be used during pregnancy only if the potential benefit justifies the potential risk to the fetus.

Nonteratogenic Effects –

Promethazine administered to a pregnant woman within two weeks of delivery may inhibit platelet aggregation in the newborn.

Labor And Delivery:

Administration of phenylephrine to patients in late pregnancy or labor may cause fetal anoxia or bradycardia by increasing contractility of the uterus and decreasing uterine blood flow.

See also "Nonteratogenic Effects."

Nursing Mothers:

It is not known whether promethazine or phenylephrine are excreted in human milk.

Caution should be exercised when promethazine and phenylephrine is administered to a nursing woman.

Pediatric Use:

Promethazine hydrochloride and phenylephrine oral solution is contraindicated for use in pediatric patients less than two years of age (see WARNINGS – Black Box Warning and Use in Pediatric Patients).

Promethazine hydrochloride and phenylephrine hydrochloride oral solution should be used with caution in pediatric patients 2 years of age and older (see WARNINGS - Use in Pediatric Patients).

Geriatric Use:

Clinical studies of promethazine hydrochloride and phenylephrine hydrochloride oral solution did not include sufficient numbers of subjects aged 65 and over to determine whether they respond differently from younger subjects. Other reported clinical experience has not identified differences in responses between the elderly and younger patients. In general, dose selection for an elderly patient should be cautious, usually starting at the low end of the dosing range, reflecting the greater frequency of decreased hepatic, renal or cardiac function, and of concomitant disease or other drug therapy.

Sedating drugs may cause confusion and over-sedation in the elderly; elderly patients generally should be started on low doses of Promethazine Hydrochloride and Phenylephrine Hydrochloride Oral Solution and observed closely.

ADVERSE REACTIONS

Promethazine:

Central Nervous System - Drowsiness is the most prominent CNS effect of this drug. Sedation, somnolence, blurred vision, dizziness; confusion, disorientation, and extrapyramidal symptoms such as oculogyric crisis, torticollis, and tongue protrusion; lassitude, tinnitus, incoordination, fatigue, euphoria, nervousness, diplopia, insomnia, tremors, convulsive seizures, excitation, catatonic-like states, hysteria. Hallucinations have also been reported.

Cardiovascular - Increased or decreased blood pressure, tachycardia, bradycardia, faintness.

Dermatologic - Dermatitis, photosensitivity, urticaria.

Hematologic - Leukopenia, thrombocytopenia, thrombocytopenic purpura, agranulocytosis.

Gastrointestinal - Dry mouth, nausea, vomiting, jaundice.

Respiratory - Asthma, nasal stuffiness, respiratory depression (potentially fatal) and apnea (potentially fatal). (See WARNINGS-Promethazine; Respiratory Depression.)

Other - Angioneurotic edema. Neuroleptic malignant syndrome (potentially fatal) has also been reported. (See WARNINGS - Promethazine; Neuroleptic Malignant Syndrome.)

Paradoxical Reactions - Hyperexcitability and abnormal movements have been reported in patients following a single administration of promethazine HCl. Consideration should be given to the discontinuation of promethazine HCl and to the use of other drugs if these reactions occur. Respiratory depression, nightmares, delirium, and agitated behavior have also been reported in some of these patients.

Phenylephrine:

Nervous System - Restlessness, anxiety, nervousness and dizziness.

Cardiovascular - Hypertension (see "WARNINGS").

Other - Precordial pain, respiratory distress, tremor, and weakness.

OVERDOSAGE

Promethazine:

Signs and symptoms of overdosage with promethazine HCl range from mild depression of the central nervous system and cardiovascular system to profound hypotension, respiratory depression, unconsciousness, and sudden death. Other reported reactions include hyperreflexia, hypertonia, ataxia, athetosis, and extensor-plantar, reflexes (Babinski reflex).

Stimulation may be evident, especially in children and geriatric patients. Convulsions may rarely occur. A paradoxical reaction has been reported in children receiving single doses of 75 mg to 125 mg orally, characterized by hyperexcitability and nightmares.

Atropine-like signs and symptoms - dry mouth, fixed dilated pupils, flushing, as well as gastrointestinal symptoms, may occur.

Phenylephrine:

Signs and symptoms of overdosage with phenylephrine include hypertension, headache, convulsions, cerebral hemorrhage, and vomiting. Ventricular premature beats and short-paroxysms of ventricular tachycardia may also occur. Headache may be a symptom of hypertension. Bradycardia may also be seen early in phenylephrine overdosage through stimulation of baroreceptors.

Treatment:

The treatment of overdosage with promethazine and phenylephrine is essentially symptomatic and supportive. Only in cases of extreme overdosage or individual sensitivity do vital signs including respiration, pulse, blood pressure, temperature, and EKG need to be monitored. Activated charcoal orally or by lavage may be given, or sodium or magnesium sulfate orally as a cathartic. Attention should be given to the reestablishment of adequate respiratory exchange through provision of a patent airway and institution of assisted or controlled ventilation. Diazepam may be used to control convulsions. Acidosis and electrolyte losses should be corrected. Note that any depressant effects of promethazine are not reversed by naloxone. Avoid analeptics which may cause convulsions.

Severe hypotension usually responds to the administration of norepinephrine or phenylephrine. EPINEPHRINE SHOULD NOT BE USED, since its use in a patient with partial adrenergic blockade may further lower the blood pressure.

Limited experience with dialysis indicates that it is not helpful.

DOSAGE AND ADMINISTRATION

It is important that promethazine hydrochloride and phenylephrine hydrochloride oral solution, USP is measured with an accurate measuring device (see Precautions-Information for Patients). A household teaspoon is not an accurate measuring device and could lead to overdosage, especially when half a teaspoon is to be measured. It is strongly recommended that an accurate measuring device be used. A pharmacist can provide instructions for measuring the correct dose.

Promethazine hydrochloride and phenylephrine hydrochloride oral solution, USP is contraindicated for children under 2 years of age (see WARNINGS –Black Box Warning and Use in Pediatric Patients).

The recommended doses are given in the following table:

Adults and Children 12 Years and Over
1 teaspoonful (5 mL) every 4 to 6 hours, not to exceed 6 teaspoonfuls (30 mL) in 24 hours.

Children 6 to Under 12 Years of Age
½ to 1 teaspoonful (2.5 to 5 mL) every 4 to 6 hours, not to exceed 6 teaspoonfuls (30 mL) in 24 hours.

Children 2 to Under 6 Years of Age
¼ to ½ teaspoonful (1.25 to 2.5 mL) every 4 to 6 hours.

HOW SUPPLIED

Promethazine Hydrochloride and Phenylephrine Hydrochloride Oral Solution, USP is a clear, pale yellow to yellow colored, citrus-flavored solution containing 6.25 mg Promethazine Hydrochloride, USP, 5 mg Phenylephrine Hydrochloride, USP and 7 percent alcohol in each teaspoonful (5 mL)
Available as:

4 fl. oz (118 mL) NDC 65162-679-86
16 fl. oz (473 mL) NDC 65162-679-90

Dispense in a tight, light-resistant container as defined in the USP.

Store at 20° to 25°C (68° to 77°F); excursions permitted to 15° to 30°C (59° to 86°F) [See USP Controlled Room Temperature].

KEEP THIS AND ALL DRUGS OUT OF THE REACH OF CHILDREN.

Rx Only

Manufactured by:
Amneal Pharmaceuticals
Branchburg, NJ 08876

Distributed by:
Amneal Pharmaceuticals
Glasgow, KY 42141

Rev. 05-2015-01